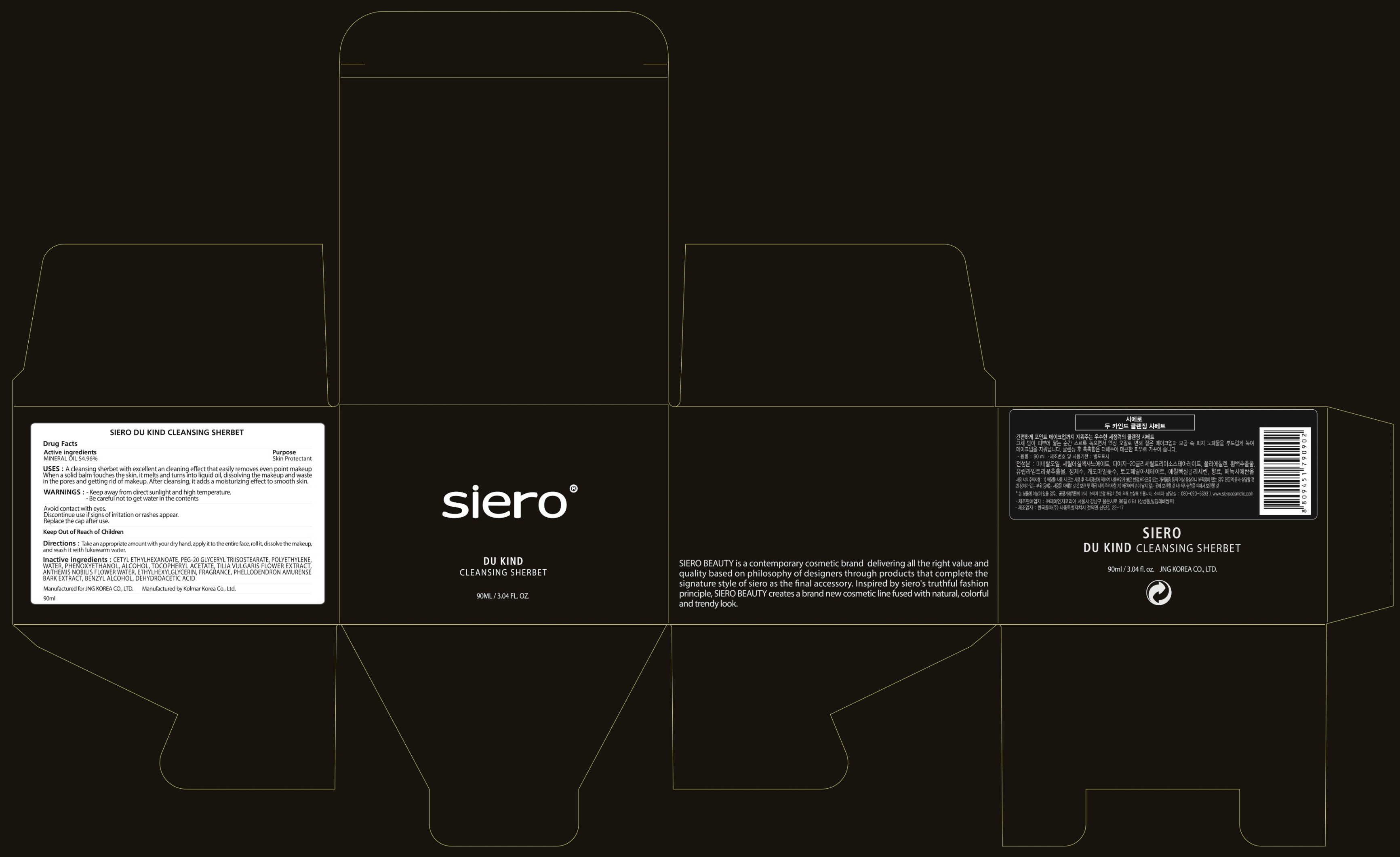 DRUG LABEL: SIERO DU KIND CLEANSING SHERBET
NDC: 71472-020 | Form: CREAM
Manufacturer: JNG KOREA CO.,LTD.
Category: otc | Type: HUMAN OTC DRUG LABEL
Date: 20170628

ACTIVE INGREDIENTS: MINERAL OIL 49.46 g/90 mL
INACTIVE INGREDIENTS: CETYL ETHYLHEXANOATE; PEG-20 GLYCERYL TRIISOSTEARATE

ACTIVE INGREDIENT

Active ingredients: MINERAL OIL 54.96%

INACTIVE INGREDIENT

Inactive ingredients: CETYL ETHYLHEXANOATE, PEG-20 GLYCERYL TRIISOSTEARATE, POLYETHYLENE, WATER, PHENOXYETHANOL, ALCOHOL, TOCOPHERYL ACETATE, TILIA VULGARIS FLOWER EXTRACT, ANTHEMIS NOBILIS FLOWER WATER, ETHYLHEXYLGLYCERIN, FRAGRANCE, PHELLODENDRON AMURENSE BARK EXTRACT, BENZYL ALCOHOL, DEHYDROACETIC ACID

PURPOSE

Purpose: Skin Protectant

WARNINGS

Warnings: - Keep away from direct sunlight and high temperature. - Be careful not to get water in the contents. Avoid contact with eyes. Discontinue use if signs of irritation or rashes appear. Replace the cap after use.

KEEP OUT OF REACH OF CHILDREN

Uses

Uses: A cleansing sherbet with excellent an cleaning effect that easily removes even point makeup When a solid balm touches the skin, it melts and turns into liquid oil, dissolving the makeup and waste in the pores and getting rid of makeup. After cleansing, it adds a moisturizing effect to smooth skin.

Directions

Directions: Take an appropriate amount with your dry hand, apply it to the entire face, roll it, dissolve the makeup, and wash it with lukewarm water.